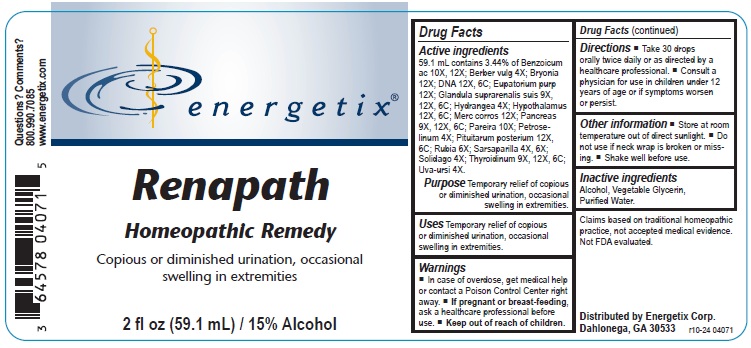 DRUG LABEL: Renapath
NDC: 64578-0103 | Form: LIQUID
Manufacturer: Energetix Corporation
Category: homeopathic | Type: HUMAN OTC DRUG LABEL
Date: 20250711

ACTIVE INGREDIENTS: CHONDRODENDRON TOMENTOSUM ROOT 10 [hp_X]/1 mL; PETROSELINUM CRISPUM 4 [hp_X]/1 mL; SUS SCROFA PITUITARY GLAND 12 [hp_X]/1 mL; RUBIA TINCTORUM ROOT 6 [hp_X]/1 mL; SARSAPARILLA 4 [hp_X]/1 mL; SOLIDAGO VIRGAUREA FLOWERING TOP 4 [hp_X]/1 mL; THYROID, BOVINE 9 [hp_X]/1 mL; ARCTOSTAPHYLOS UVA-URSI LEAF 4 [hp_X]/1 mL; BENZOIC ACID 10 [hp_X]/1 mL; BERBERIS VULGARIS ROOT BARK 4 [hp_X]/1 mL; BRYONIA ALBA ROOT 12 [hp_X]/1 mL; HERRING SPERM DNA 12 [hp_X]/1 mL; EUTROCHIUM PURPUREUM ROOT 12 [hp_X]/1 mL; SUS SCROFA ADRENAL GLAND 9 [hp_X]/1 mL; HYDRANGEA ARBORESCENS ROOT 4 [hp_X]/1 mL; BOS TAURUS HYPOTHALAMUS 12 [hp_X]/1 mL; MERCURIC CHLORIDE 12 [hp_X]/1 mL; SUS SCROFA PANCREAS 9 [hp_X]/1 mL
INACTIVE INGREDIENTS: WATER; GLYCERIN; ALCOHOL

Renapath

ACTIVE INGREDIENT

Active ingredients 59.1 mL contains 3.44% of: Benzoicum ac 10X, 12X; Berber vulg 4X; Bryonia 12X; DNA 12X, 6C; Eupatorium purp 12X; Glandula suprarenalis suis 9X, 12X, 6C; Merc corros 12X; Pancreas 9X, 12X, 6C; Pareira 10X, Petroselinum 4X; Pituitarum posterium 12X 6C; Rubia 6X; Sarsaparilla 4X, 6X; Solidago 4X; Thyroidinum 9X, 12X, 6C; Uva-ursi 4X.

Claims based on traditional homeopathic practice, not accepted medical evidence. Not FDA evaluated.

INDICATIONS AND USAGE

Uses Temporary relief of copious or diminished urination, occasional swelling in extremities.

Warnings

In case of overdose, get medical help or contact a Poison Control Center right away.
If pregnant or breast feeding,ask a health professional before use.

Keep out of reach of children.

Directions

- Take 30 drops orally twice daily or as directed by a healthcare professional.
- Consult a physician for use in children under 12 years of age or if symptoms worsen or persist.

Other information

- Store at room temperature out of direct sunlight.
- Do not use if neck wrap is broken or missing.
- Shake well before use.

Inactive ingredients

Alcohol, Vegetable Glycerin, Purified Water.

QUESTIONS

Distributed by
Energetix Corp.
Dahlonega, GA 30533

Questions? 800.990.7085
www.energetix.com

PACKAGE LABEL

energetix
Renapath
Homeopathic Remedy
Copious or diminished urination, occasional
swelling in extremities.
2 fl oz (59.1 mL) / 15% Alcohol

PURPOSE

Purpose Temporary relief of copious or diminished urination, occasional swelling in extremities.